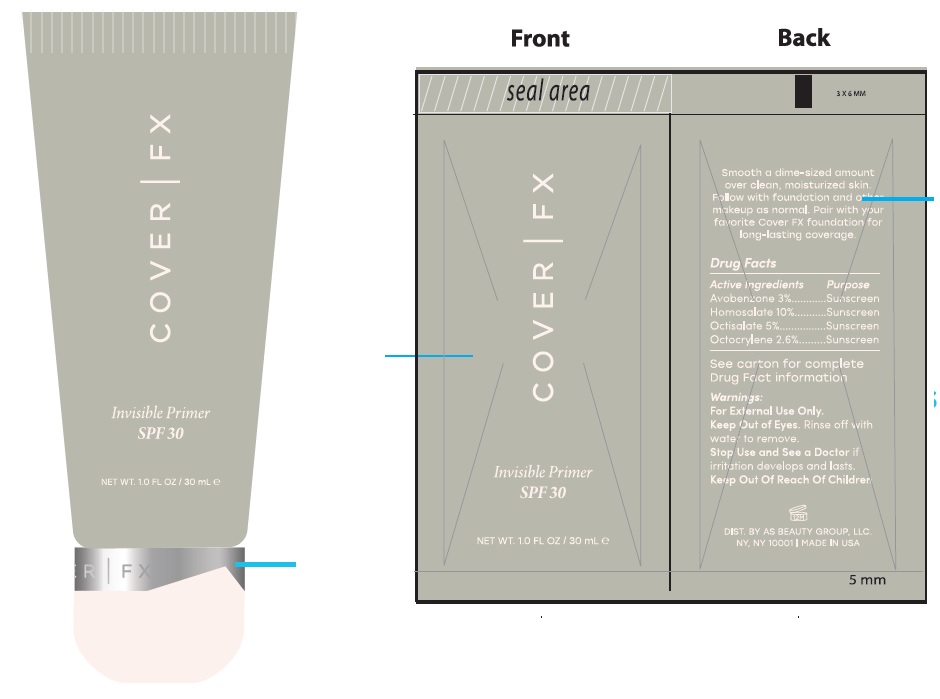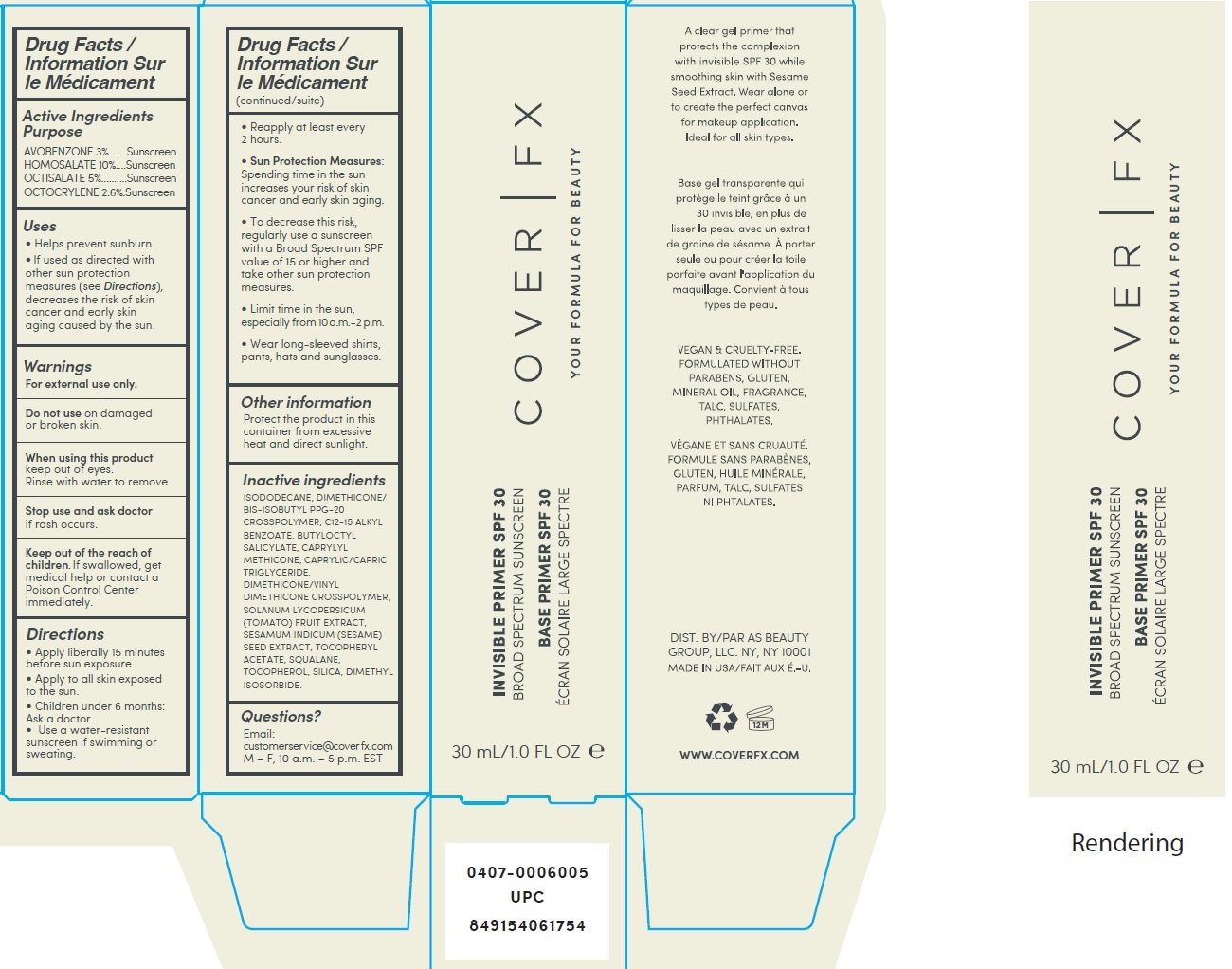 DRUG LABEL: Cover FX Invisible Primer SPF30
NDC: 68577-105 | Form: LOTION
Manufacturer: Cosmax Usa, Corporation
Category: otc | Type: HUMAN OTC DRUG LABEL
Date: 20241226

ACTIVE INGREDIENTS: AVOBENZONE 30 mg/1 mL; HOMOSALATE 100 mg/1 mL; OCTISALATE 50 mg/1 mL; OCTOCRYLENE 26 mg/1 mL
INACTIVE INGREDIENTS: ISODODECANE; DIMETHICONE/BIS-ISOBUTYL PPG-20 CROSSPOLYMER; ALKYL (C12-15) BENZOATE; BUTYLOCTYL SALICYLATE; CAPRYLYL TRISILOXANE; MEDIUM-CHAIN TRIGLYCERIDES; TOMATO; SESAME SEED; .ALPHA.-TOCOPHEROL ACETATE; SQUALANE; TOCOPHEROL; SILICON DIOXIDE; DIMETHYL ISOSORBIDE

Cover FX Invisible Primer SPF30

Active Ingredients

AVOBENZONE 3%
HOMOSALATE 10%
OCTISALATE 5%

OCTOCRYLENE 2.6%

Purpose

Sunscreen

Uses

- Helps prevent sunburn.
- If used as directed with other sun protection measures (see Directions), decreases the risk of skin cancer and early skin aging caused by the sun.

Warnings

For external use only.

Do not use

on damaged or broken skin.

When using this product

keep out of eyes. Rinse with water to remove.

Stop use and ask doctor

if rash occurs.

Keep out of the reach of children.

If swallowed, get medical help or contact a Poison Control Center immediately.

Directions

- Apply liberally 15 minutes before sun exposure.
- Apply to all skin exposed to the sun.
- Children under 6 months: Ask a doctor.
- Use a water-resistant sunscreen if swimming or sweating.
- Reapply at least every 2 hours.
- Sun Protection Measures: Spending time in the sun increases your risk of skin cancer and early skin aging.
- To decrease this risk, regularly use a sunscreen with a Broad Spectrum SPF value of 15 or higher and take other sun protection measures.
- Limit time in the sun, especially from 10 a.m.-2 p.m.
- Wear long-sleeved shirts, pants, hats and sunglasses.

Other information

Protect the product in this container from excessive heat and direct sunlight.

Inactive ingredients

ISODODECANE, DIMETHICONE/ BIS-ISOBUTYL PPG-20 CROSSPOLYMER, C12-15 ALKYL BENZOATE, BUTYLOCTYL SALICYLATE, CAPRYLYL METHICONE, CAPRYLIC/CAPRIC TRIGLYCERIDE, DIMETHICONE/VINYL DIMETHICONE CROSSPOLYMER, SOLANUM LYCOPERSICUM (TOMATO) FRUIT EXTRACT, SESAMUM INDICUM (SESAME) SEED EXTRACT, TOCOPHERYL ACETATE, SQUALANE, TOCOPHEROL, SILICA, DIMETHYL ISOSORBIDE.

Questions?

Email: customerservice@cover fx.com M – F, 10 a.m. – 5 p.m. EST